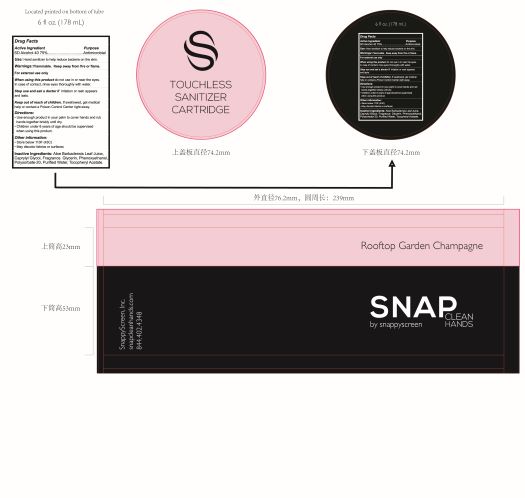 DRUG LABEL: Hand Sanitizer
NDC: 58133-959 | Form: AEROSOL, SPRAY
Manufacturer: Cosmetic Specialty Labs, Inc.
Category: otc | Type: HUMAN OTC DRUG LABEL
Date: 20210830

ACTIVE INGREDIENTS: ALCOHOL 75 mL/100 mL
INACTIVE INGREDIENTS: POLYSORBATE 20; PHENOXYETHANOL; WATER; ALPHA-TOCOPHEROL ACETATE; CAPRYLYL GLYCOL; GLYCERIN; ALOE VERA LEAF

This is a hand sanitizer manufactured according to the Temporary Policy for Preparation of Certain Alcohol-Based Hand Sanitizer Products During the Public Health Emergency (CoViD-19); Guidance for Industry.

The hand sanitizer is manufactured using only the following United States Pharmacopoeia (USP) grade ingredients in the preparation of the product (percentage in final product formulation) consistent with World Health Organization (WHO) recommendations:

1. Alcohol (ethanol) (USP or Food Chemical Codex (FCC) grade) (75%, volume/volume (v/v)) in an aqueous solution denatured according to Alcohol and Tobacco Tax and Trade Bureau regulations in 27 CFR part 20.
2. Aloe Barbadenis Leaf Juice.
3. Caprylyl Glycol.
4. Glycerin.
5. Phenoxyethanol.
6. Polysorate-20.
7. Purified Water.
8. Tocopheryl Acetate.

The firm does not add other active or inactive ingredients. Different or additional ingredients may impact the quality and potency of the product.

Active Ingredient

SD Alcohol 40 75%

PURPOSE

Antimicrobial

Use

Hand Sanitizer to help reduce bacteria on the skin.

Use

subsection identifying number is Sequence 4.

change incorporated in the label on 4/2021.

Warnings

Flammable. Keep away from fire or flame. For external use only.

When using this product do not use in or near the eyes. In case of contact, rinse eyes thoroughtly with water.

Stop use and ask a doctor if irritation or rash appears and lasts.

Keep out of reach of children. If swallowed, get medical help or contact a Poison Center right away.

Directions

- Use enough product in your palm to cover hands and rub hands together biskly until dry.
- Children under 6 years of age should be supervised when using this product.

Directions

Identifying number of subsection is 9.

change incorporated in the label 04/2021.

Other information

- Store below 110F (43C)
- May discolor fabrics or surfaces

Inactive ingredients

Aloe Barbadensis Leaf Juice, Caprylyl Glycol, Fragrance, Glycerin, Phenoxyethanol, Polysorbate-20, Purified Water, Tocopheryl Acetate.

Package Label - Principal Display Panel

NDC:58133-959-62